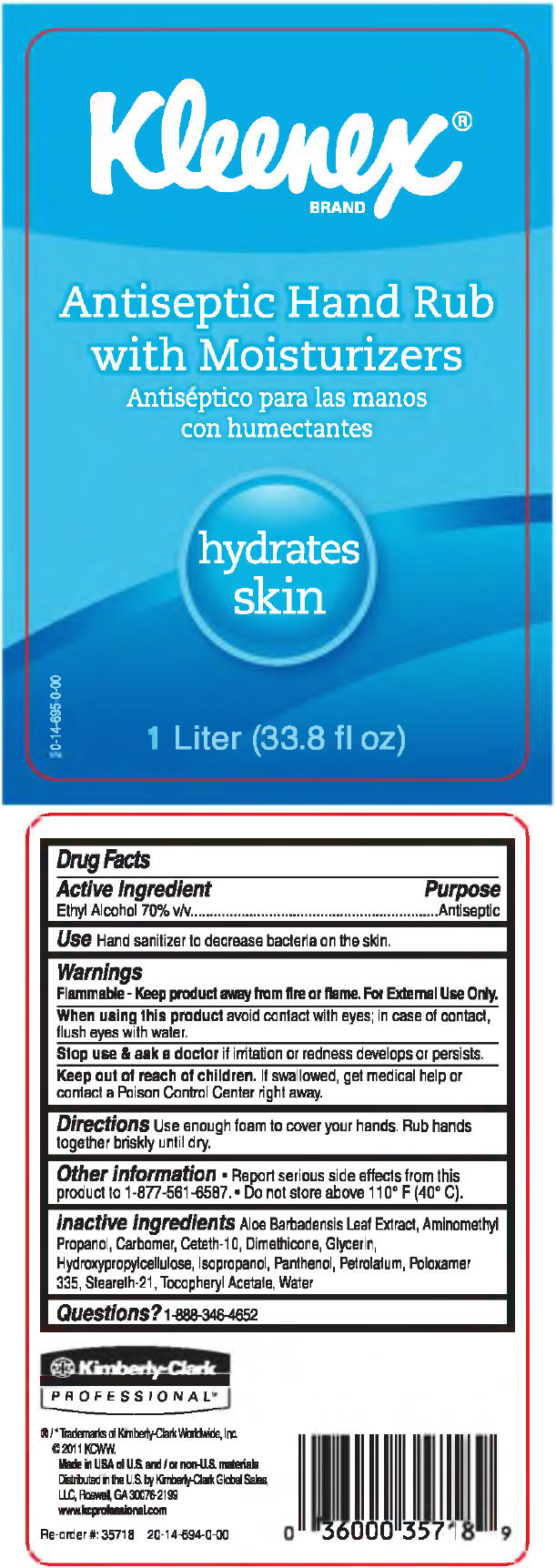 DRUG LABEL: KLEENEX Antiseptic Hand Rub with Moisturizers
NDC: 55118-580 | Form: SOLUTION
Manufacturer: Kimberly-Clark Corporation
Category: otc | Type: HUMAN OTC DRUG LABEL
Date: 20141103

ACTIVE INGREDIENTS: Alcohol 0.7 L/1 L
INACTIVE INGREDIENTS: Water; Glycerin; Dimethicone; Liquid Petroleum; Aminomethylpropanol; Hydroxypropyl Cellulose (Type H); Ceteth-10; Steareth-21; Aloe Vera Leaf; Panthenol; Poloxamer 335; .Alpha.-Tocopherol Acetate

KLEENEX® Antiseptic Hand Rub with Moisturizers

Drug Facts

Active Ingredient

Ethyl Alcohol 70% v/v

Purpose

Antiseptic

Use

Hand sanitizer to decrease bacteria on the skin.

Warnings

DO NOT USE

Flammable - Keep product away from fire or flame. For External Use Only.

When using this product avoid contact with eyes; in case of contact, flush eyes with water.

Stop use & ask a doctor if irritation or redness develops or persists.

Keep out of reach of children. If swallowed, get medical help or contact a Poison Control Center right away.

Directions

Use enough foam to cover your hands. Rub hands together briskly until dry.

Other information

- Report serious side effects from this product to 1-877-561 -6587
- Do not store above 110° F (40° C).

inactive ingredients

Aloe Barbadensis Leaf Extract, Aminomethyl Propanol, Carbomer, Ceteth-10, Dimethicone, Glycerin, Hydroxypropylcellulose, Isopropanol, Panthenol, Petrolatum, Poloxamer 335, Steareth-21, Tocopheryl Acetate, Water

Questions?

1-888-346-4652

Distributed in the U.S. by Kimberly-Clark Global Sales,
LLC, Roswell, GA 30076-2199

PRINCIPAL DISPLAY PANEL - 1 Liter Container Label

Kleenex®
BRAND

Antiseptic Hand Rub
with Moisturizers

hydrates
skin

1 Liter (33.8 fl oz)

20-14-695-0-00